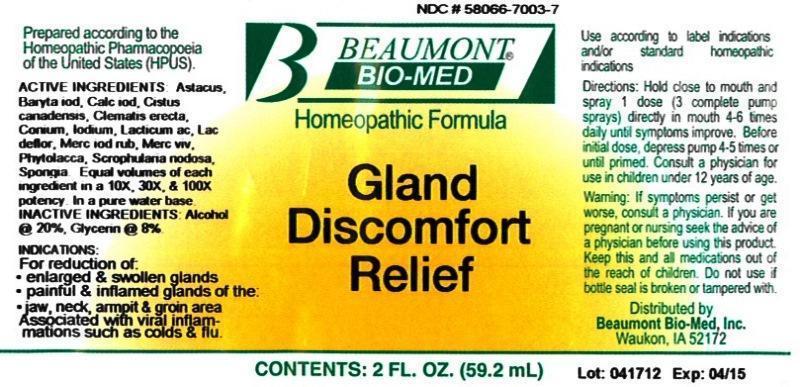 DRUG LABEL: Gland Discomfort Relief
NDC: 58066-7003 | Form: LIQUID
Manufacturer: Beaumont Bio Med
Category: homeopathic | Type: HUMAN OTC DRUG LABEL
Date: 20150108

ACTIVE INGREDIENTS: ASTACUS ASTACUS 10 [hp_X]/59.2 mL; BARIUM IODIDE 10 [hp_X]/59.2 mL; CALCIUM IODIDE 10 [hp_X]/59.2 mL; HELIANTHEMUM CANADENSE 10 [hp_X]/59.2 mL; CLEMATIS RECTA FLOWERING TOP 10 [hp_X]/59.2 mL; CONIUM MACULATUM FLOWERING TOP 10 [hp_X]/59.2 mL; IODINE 10 [hp_X]/59.2 mL; LACTIC ACID, DL- 10 [hp_X]/59.2 mL; SKIM MILK 10 [hp_X]/59.2 mL; MERCURIC IODIDE 10 [hp_X]/59.2 mL; MERCURY 10 [hp_X]/59.2 mL; PHYTOLACCA AMERICANA ROOT 10 [hp_X]/59.2 mL; SCROPHULARIA NODOSA 10 [hp_X]/59.2 mL; SPONGIA OFFICINALIS SKELETON, ROASTED 10 [hp_X]/59.2 mL
INACTIVE INGREDIENTS: WATER; ALCOHOL; GLYCERIN

Gland Discomfort Relief

ACTIVE INGREDIENT

HPUS active ingredients: Astacus fluviatilis, Baryta iodata, Calcarea iodata, Cistus canadensis, Clematis erecta, Conium maculatum, Iodium, Lacticum acidum, Lac defloratum, Mercurius iodatus ruber, Mercurius vivus, Phytolacca decandra, Scrophularia nodosa, Spongia tosta. Equal volumes of each ingredient in 10X, 30X, 100X potencies.

INACTIVE INGREDIENT

Inactive Ingredients: Alcohol @ (20% v/v), Glycerin @ (8% v/v), in a pure water base.

INDICATIONS AND USAGE

Indications: For temporary relief of: enlarged and swollen glands, painful and inflamed glands of the jaw, neck, armpit and groin area. Associated with viral inflammations such as colds and flu.

Directions:

- Hold close to mouth and spray 1 dose (3 complete pump sprays) directly in mouth 4-6 times daily until symptoms improve.
- Before initial dose, depress pump 4-5 times or until primed.
- Consult a physician for use in children under 12 years of age.

Use according to label indications and/or standard homeopathic indications

WARNINGS

Warnings: If symptoms persist or get worse, consult a physician. If you are pregnant or nursing seek the advice of a physician before using this product. Keep this and all medications out of the reach of children. Do not use if bottle seal is broken or tampered with.

- Keep out of reach of children.

PURPOSE

For temporary relief of:

- enlarged and swollen glands
- painful and inflamed glands of the jaw, neck, and groin area

Associated with viral inflammations such as colds and flu.